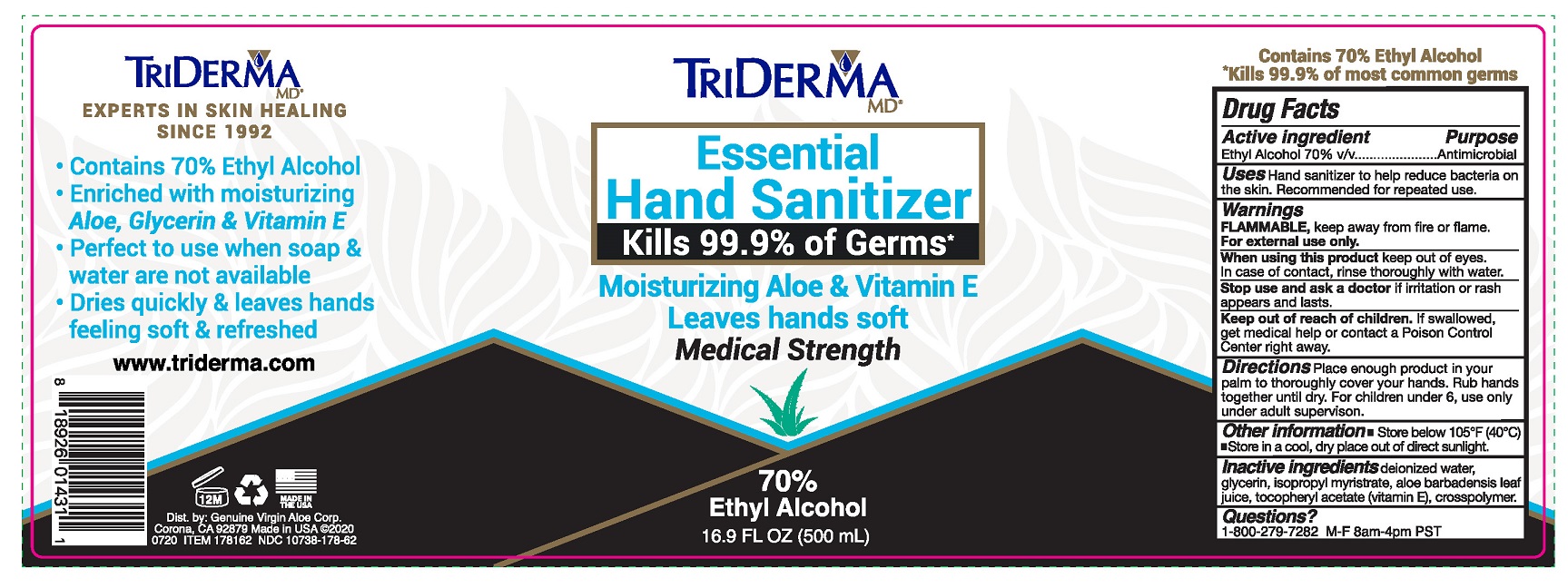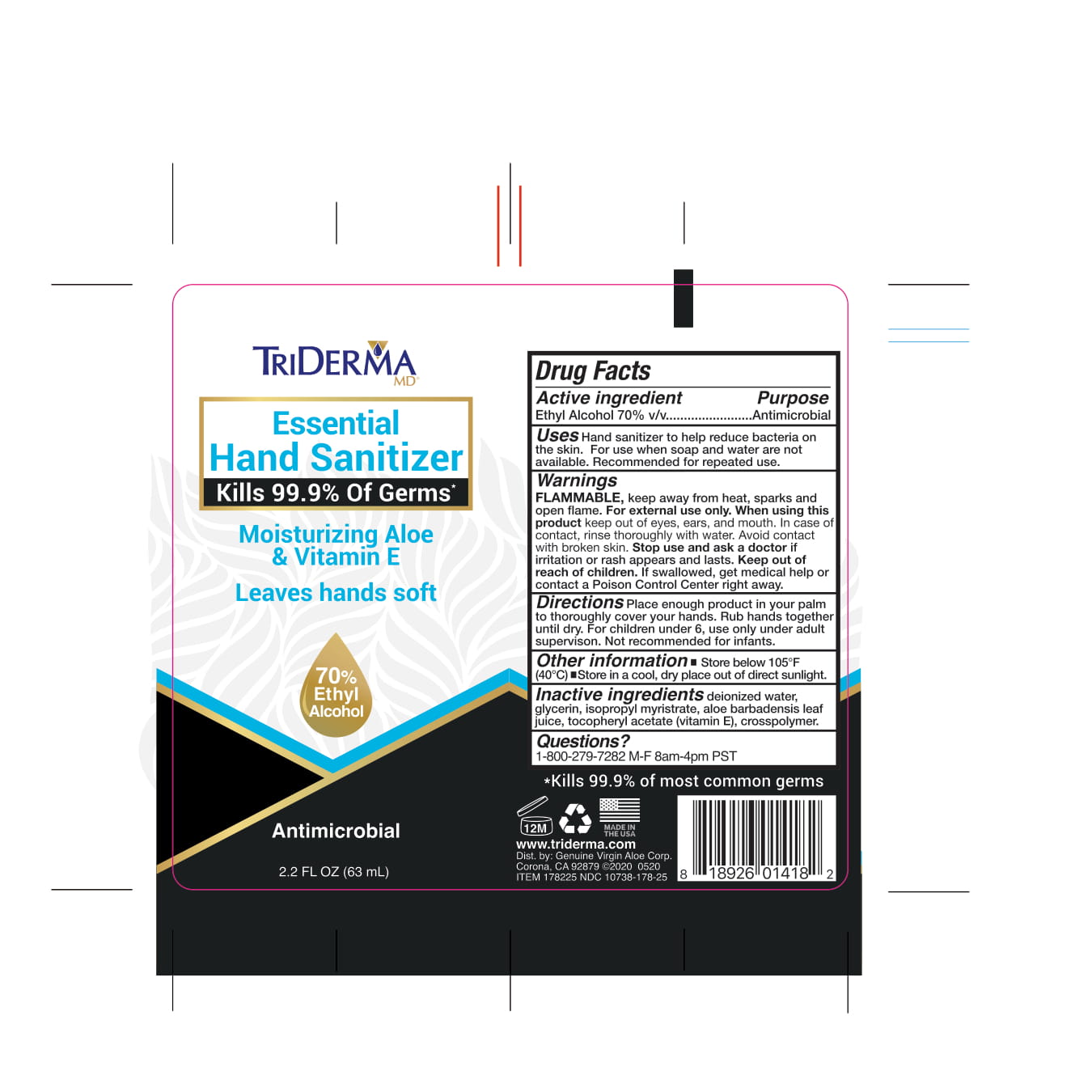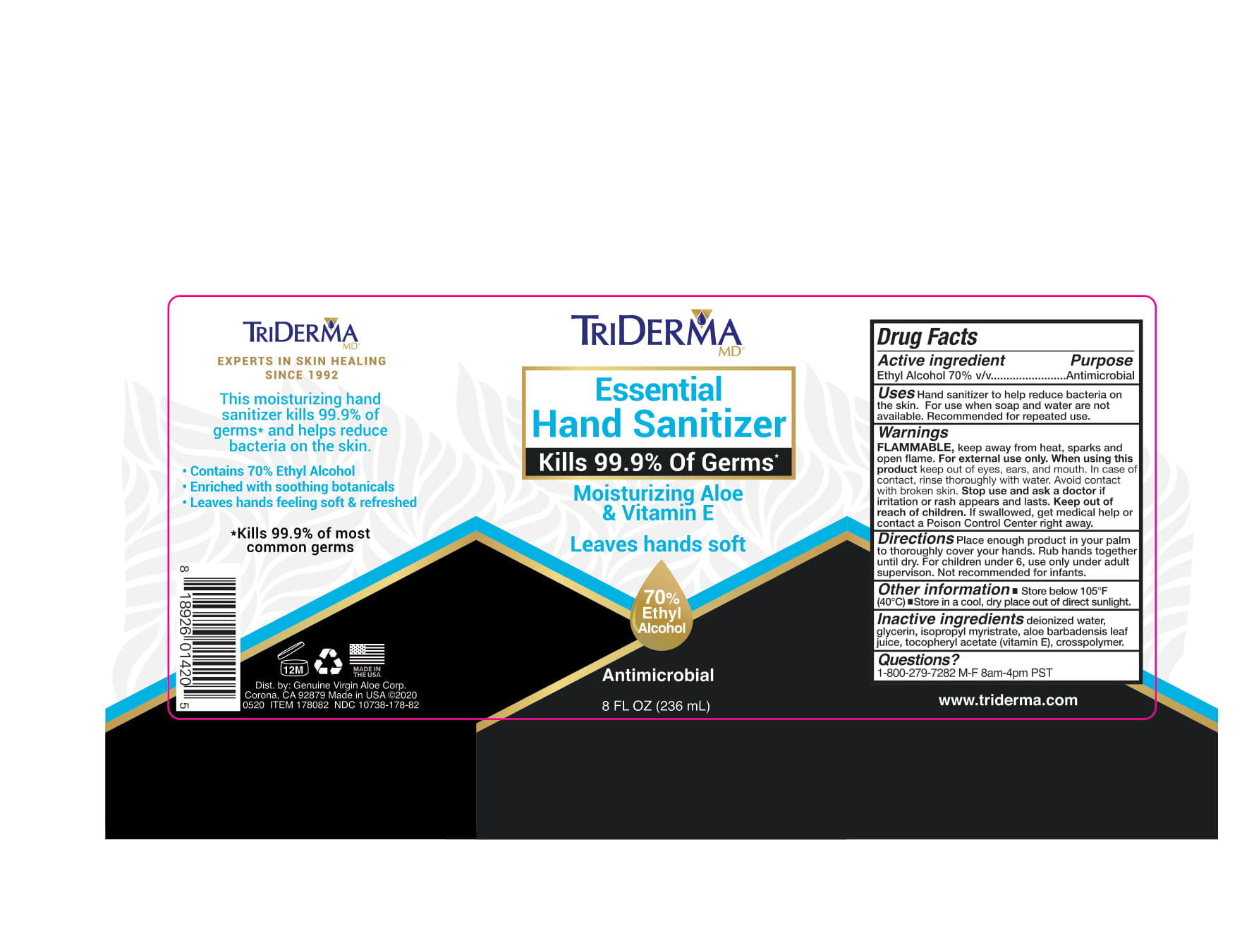 DRUG LABEL: Triderma Essential Hand Sanitizer
NDC: 10738-178 | Form: GEL
Manufacturer: Genuine Virgin Aloe Corporation
Category: otc | Type: HUMAN OTC DRUG LABEL
Date: 20220114

ACTIVE INGREDIENTS: ALCOHOL 0.7 mL/1 mL
INACTIVE INGREDIENTS: WATER; ISOPROPYL MYRISTATE; .ALPHA.-TOCOPHEROL ACETATE, DL-; GLYCERIN; ALOE VERA LEAF

Triderma MD® Essential Hand Sanitizer 70%

Active ingredient

Ethyl Alcohol 70% v/v

Purpose

Antimicrobial

Uses

Hand sanitizer to help reduce bacteria on the skin. For use when soap and water are not available. Recommended for repeated use.

Warnings

Flammable, keep away from fire or flame.

For external use only

When using this product

keep out of eyes,ears, and mouth. In case of contact, rinse thoroughly with water. Avoid contact with broken skin.

Stop use and ask a doctor

if irritation or rash appears and lasts.

Keep out of reach of children.

if swallowed, get medical help or contact a Poison Control Center right away

Directions

Place enough product in your palm to thoroughly cover your hands. Rub hands together untill dry. For children under 6, use only under adult supervision. Not recommended for infants.

Other information

- Store below 105° F (40° C)
- May discolor certain fabrics or surfaces; harmful to wood finishes and plastics

Inactive ingredients

deionized water, glycerin, isopropyl myristrate, aloe barbadensis leaf juice, tocopheryl acetate (vitamin E), crosspolymer

Questions?

1-800-279-7282 M-F 8am-4pm PST

PACKAGE LABEL

Triderma MD®

Essential Hand Sanitizer

Kills 99.9% Of Germs*

Moisturizing Aloe & Vitamin E

Leaves hands soft

70% Ethyl Alcohol

Antimicrobial

Experts In Skin Healing Since 1992

This moisturizing hand sanitizer kills 99.9% of germs* and helps reduce bacteria on the skin.

Contains 70% Ethyl Alcohol

Enriched with soothing botanicals

Leaves hands feeling soft & refreshed

*Kills 99.9% most common germs

Dist by: Genuine Virgin Aloe Corp.

Corona, CA 92879 Made in USA ©2020

0520 Item 178082 NDC 10738-178-82

Item 178225 NDC 10738-178-25

2.2 fl. oz. (63 mL)

8 fl. oz (236 mL)

16.9 Fl. Oz.